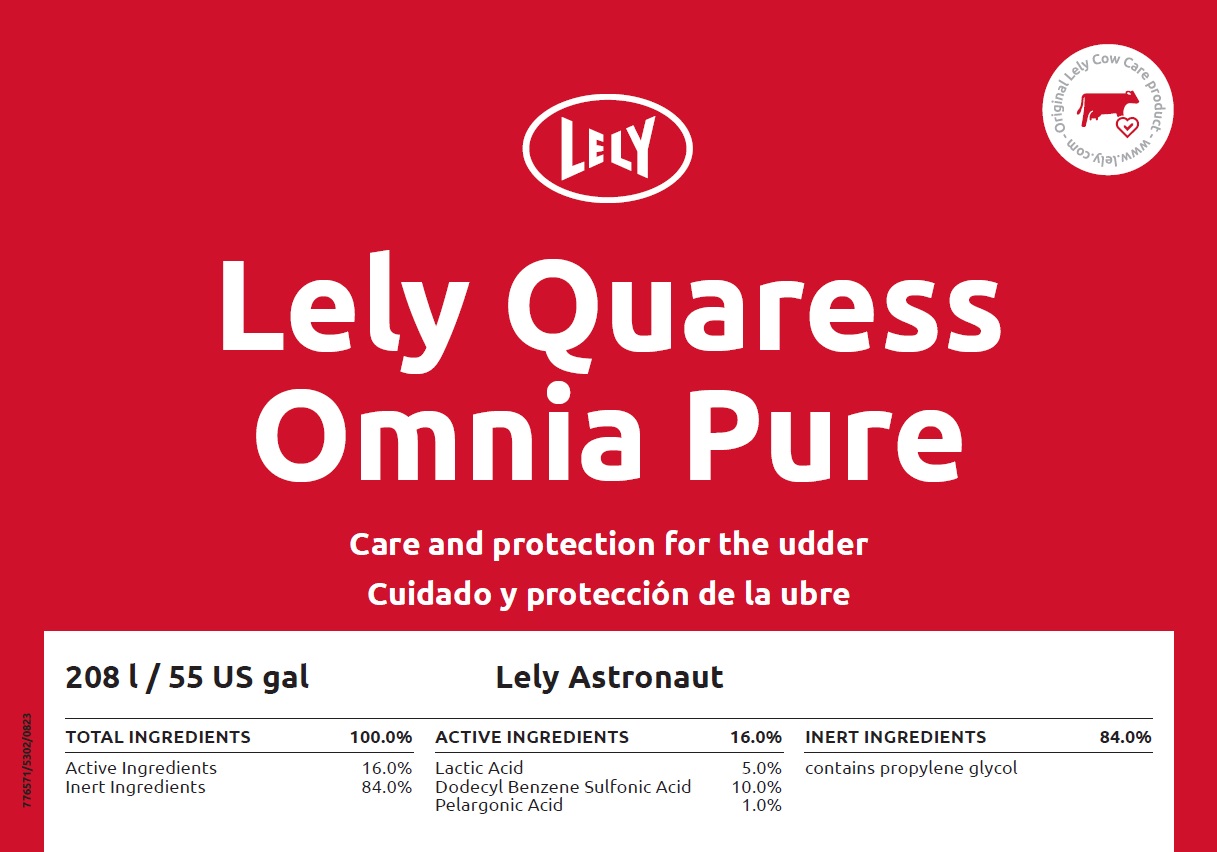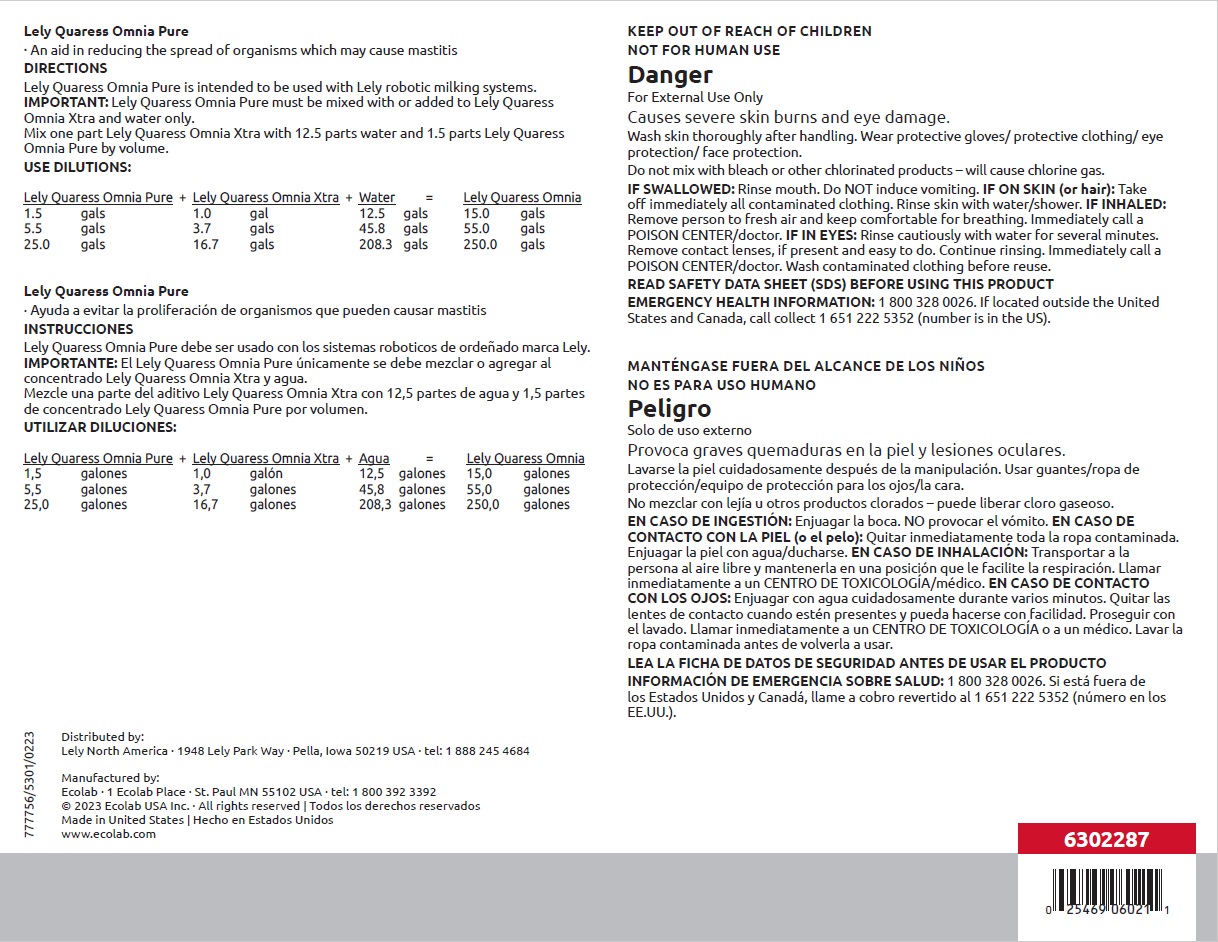 DRUG LABEL: Lely Quaress Omnia Pure
NDC: 86190-005 | Form: SOLUTION
Manufacturer: Lely North America, Inc.
Category: animal | Type: OTC ANIMAL DRUG LABEL
Date: 20230922

ACTIVE INGREDIENTS: LACTIC ACID 50 mg/1 mL; DODECYLBENZENESULFONIC ACID 100 mg/1 mL; PELARGONIC ACID 10 mg/1 mL
INACTIVE INGREDIENTS: WATER; PROPYLENE GLYCOL

KEEP OUT OF REACH OF CHILDREN

NOT FOR HUMAN USE

Danger

For External Use Only

Causes severe skin burns and eye damage.

Wash skin thoroughly after handling. Wear protective gloves/ protective clothing/ eye protection/ face protection.

Do not mix with bleach or other chlorinated products – will cause chlorine gas.

DIRECTIONS

Lely Quaress Omnia Pure is intended to be used with Lely robotic milking systems. IMPORTANT: Lely Quaress Omnia Pure must be mixed with or added to Lely Quaress Omnia Xtra and water only.

Mix one part Lely Quaress Omnia Xtra with 12.5 parts water and 1.5 parts Lely Quaress Omnia Pure by volume.

USE DILUTIONS
Lely Quaress Omnia Pure + | Lely Quaress Omnia Xtra + | Water | = Lely Quaress Omnia
1.5 gals | 1.0 gals | 12.5 gals | 15.0 gals
5.5 gals | 3.7 gals | 45.8 gals | 55.0 gals
25.0 gals | 16.7 gals | 208.3 gals | 250.0 gals

OTHER SAFETY INFORMATION

IF SWALLOWED: Rinse mouth. Do NOT induce vomiting. IF ON SKIN (or hair): Take

off immediately all contaminated clothing. Rinse skin with water/shower. IF INHALED: Remove person to fresh air and keep comfortable for breathing. Immediately call a POISON CENTER/doctor. IF IN EYES: Rinse cautiously with water for several minutes. Remove contact lenses, if present and easy to do. Continue rinsing. Immediately call a POISON CENTER/doctor. Wash contaminated clothing before reuse.

READ SAFETY DATA SHEET (SDS) BEFORE USING THIS PRODUCT

EMERGENCY HEALTH INFORMATION: 1 800 328 0026. If located outside the United States and Canada, call collect 1 651 222 5352 (number is in the US).

Principal display panel and representative label

Lely

Lely Quaress

Omnia Pure

Care and protection for the udder

208 l / 55 US gal Lely Astronaut

TOTAL INGREDIENTS 100.0% | ACTIVE INGREDIENTS 16.0% | INERT INGREDEINTS 84.0%
Active Ingredients 16.0% | Lactic Acid 5.0% | contains propylene glycol
Inert Ingredients 84.0% | Dodecyl Benzene Sulfonic Acid 10.0%
 | Pelargonic Acid 1.0%

Distributed by:

Lely North America · 1948 Lely Park Way · Pella, Iowa 50219 USA · tel: 1 888 245 4684

Manufactured by:

Ecolab · 1 Ecolab Place · St. Paul MN 55102 USA · tel: 1 800 392 3392

© 2023 Ecolab USA Inc. · All rights reserved | Todos los derechos reservados

Made in United States | Hecho en Estados Unidos

www.ecolab.com